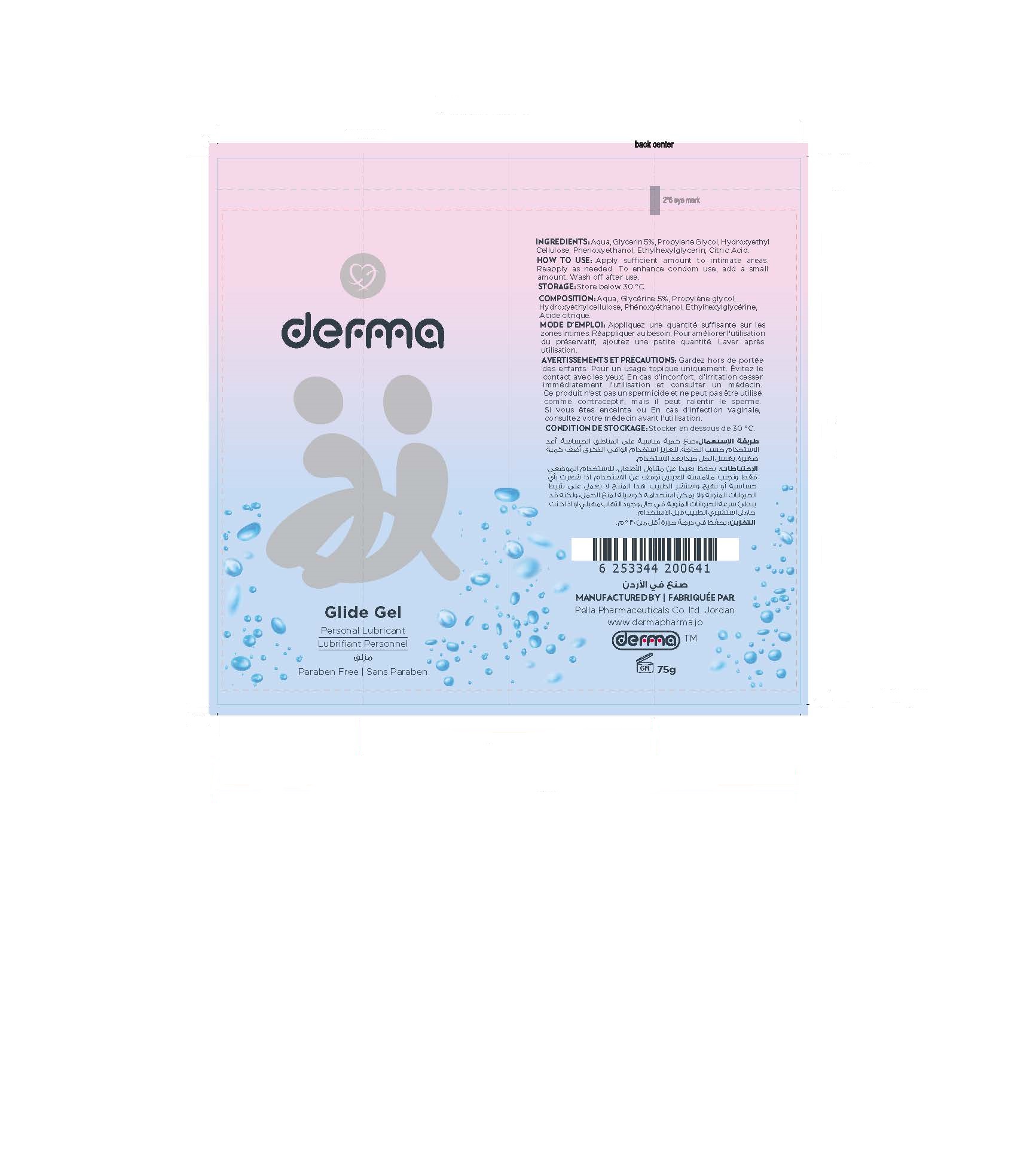 DRUG LABEL: Derma Glide
NDC: 82160-641 | Form: GEL
Manufacturer: Pella Pharmaceuticals Co. Ltd
Category: otc | Type: HUMAN OTC DRUG LABEL
Date: 20241231

ACTIVE INGREDIENTS: GLYCERIN 50 mg/1 g
INACTIVE INGREDIENTS: ETHYLHEXYLGLYCERIN; PHENOXYETHANOL; WATER; CITRIC ACID MONOHYDRATE; PROPYLENE GLYCOL; HYDROXYETHYL CELLULOSE, UNSPECIFIED

Derma Glide Gel

Forms and Presentation

Gel: Tube, 75 g

Active Ingredients

Glycerin

Inactive Ingredients

Aqua, Propylene Glycol, Hydroxyethylcellulose, Phenoxyethanol, Ethylhexylglycerin, Citric Acid.

Purpose

Personal Lubricant

Properties

Derma Glide gel is gentle, transparent, greaseless water based gel, matches the pH of the vagina.

Does not contain fragrances, colorant, parabens, and silicone oils.

Indication

Derma Glide gel is a personal lubricant for him and her to apply it onto intimate areas, intended to lubricate and moisturize, to enhance the ease and comfort of intimate sexual activity and supplement the body's natural lubrication.

Precuations

Keep out of reach of children

Warnings

- For topical use only.
- Avoid contact with the eyes.
- If discomfort or irritation or discomfort occurs, discontinue use immediately and consult a physician.
- In case of vaginal infection, consult your doctor before use.
- If you are pregnant consult your doctor before use.
- This Product is not a spermicide and cannot be used as a contraceptive, but it may slow sperm down, so if you are trying to have a baby, talk to your doctor before use.
- Very slippery on surfaces, clean spills immediately.

Contraindication

Hypersensitivity to any of the components

Side Effects

There are no known side effects

Dosage and Administration

Remove seal from tube opening before initial use. Apply sufficient amount to intimate areas. Reapply as needed. To enhance condom use, add a small amount to the inner and outer surfaces. Wash off after use.

Storage Conditions

Store below 30◦C